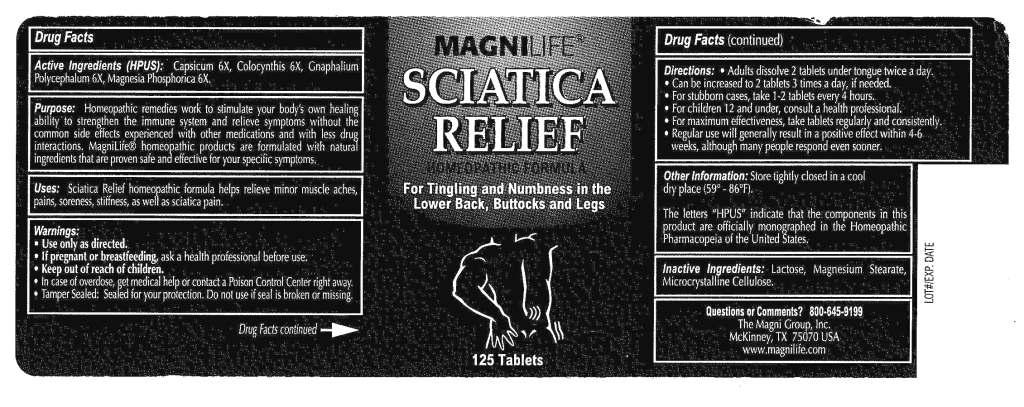 DRUG LABEL: Sciatica Relief
NDC: 57520-0581 | Form: TABLET
Manufacturer: Apotheca Company
Category: homeopathic | Type: HUMAN OTC DRUG LABEL
Date: 20110317

ACTIVE INGREDIENTS: CAPSICUM 6 [hp_X]/1 1; CITRULLUS COLOCYNTHIS FRUIT PULP 6 [hp_X]/1 1; PSEUDOGNAPHALIUM OBTUSIFOLIUM 6 [hp_X]/1 1; MAGNESIUM PHOSPHATE, DIBASIC TRIHYDRATE 6 [hp_X]/1 1
INACTIVE INGREDIENTS: LACTOSE; MAGNESIUM STEARATE; CELLULOSE, MICROCRYSTALLINE

Sciatica Relief

ACTIVE INGREDIENT

ACTIVE INGREDIENTS: Capsicum annuum 6X, Colocynthis 6X, Gnaphalium polycephalum 6X, Magnesia phosphorica 6X.

PURPOSE

USES: Temporarily relieves these symptoms due to sciatica:

Intense pain in the buttocks and lower back

Pain and numbness in the legs and feet

Tingling sensations

WARNINGS

WARNINGS: If pregnant or breastfeeding, ask a health professional before use.

Keep out of reach of children. In case of overdose, get medical help or contact a Poison Control Center right away.

OTHER INFORMATION: Tamper Sealed: Sealed for your protection. Do not use if seal is broken or missing.

Store tightly closed in a cool, dry place (59 - 86 F).

The letters "HPUS" indicate that the components in this product are officially monographed in the Homeopathic Pharmacopeia of the United States.

DOSAGE AND ADMINISTRATION

DIRECTIONS: Adults and children 12 years and above: Dissolve 2 tablets under tongue 2 to 3 times daily or as directed by a physician.

Children under 12 years: Consult a physician

INACTIVE INGREDIENT

INACTIVE INGREDIENTS: Lactose, Magnesium stearate, Microcrystaline cellulose.

KEEP OUT OF REACH OF CHILDREN. In case of overdose, get medical help or contact a Poison Control Center right away.

INDICATIONS AND USAGE

USES: Temporarily relieves these symptoms due to sciatica:

Intense pain in the buttocks and lower back

Pain and numbness in the legs and feet

Tingling sensations

QUESTIONS

Dist. by:

The Magni Group, Inc.

McKinney, TX 75071 USA

www.magnilife.com

1-800-645-9199

PACKAGE LABEL

NDC 57520-0581-1

MAGNILIFE

SCIATICA RELIEF

HOMEOPATHIC

For tingling and Numbness in the Lower Back, Buttocks and Legs

125 Tablets